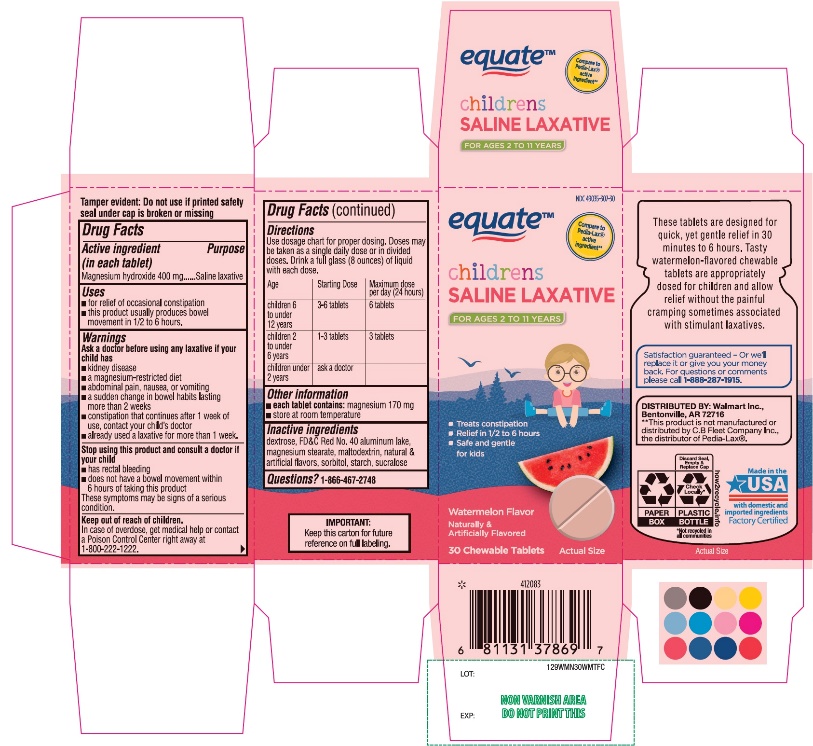 DRUG LABEL: Childrens Oral Saline Laxative
NDC: 49035-307 | Form: TABLET, CHEWABLE
Manufacturer: WAL-MART STORES,INC.,
Category: otc | Type: HUMAN OTC DRUG LABEL
Date: 20251027

ACTIVE INGREDIENTS: MAGNESIUM HYDROXIDE 400 mg/1 1
INACTIVE INGREDIENTS: DEXTROSE, UNSPECIFIED FORM; FD&C RED NO. 40; WATERMELON; MAGNESIUM STEARATE; MALTODEXTRIN; SORBITOL; STARCH, CORN; SUCRALOSE

Children’s Oral Saline Laxative Chewable Tablets

Active Ingredient

Magnesium hydroxide 400 mg

Purpose

Saline laxative

Uses

- for relief of occasional constipation
- this product usually produces bowel movement in 1/2 to 6 hours

Warnings

Ask a doctor before using any laxative if child has

- kidney disease
- a magnesium-restricted diet
- abdominal pain, nausea or vomiting
- a sudden change in bowel habits lasting more than 2 weeks
- constipation continues after 1 week of use, contact your child's doctor
- already used a laxative for more than 1 week

Stop use and consult a doctor if your child has

- has rectal bleeding
- does not have a bowel movement within 6 hours of taking this product

These symptoms may indicate a serious condition.

Keep out of reach of children

In case of overdose, get medical help or contact a Poison Control Center right away at 1-800-222-1222.

Directions

Use dosage chart for proper dosing. Doses may be taken as a single daily dose or in divided doses. Drink a full glass (8 ounces) of liquid with each dose.

Age | Starting dose | Maximum dose per day
children 6 to under 12 years | 3-6 tablets | 6 tablets
children 2 to under 6 years | 1-3 tablets | 3 tablets
children under 2 years | ask a doctor

Other information

- each tablet contains: magnesium 170 mg
- store at room temperature

Inactive ingredients

dextrose, FD&C Red 40 aluminum lake, magnesium stearate, maltodextrin, natural & artificial flavor, sorbitol, starch, sucralose.

Questions or comments?

1-866-467-2748

PRINCIPAL DISPLAY PANEL

*Compare to the active ingredient in Pedia-Lax®

NDC# 49035-307-30

Children’s Oral Saline Laxative

- Treats constipation
- Relief in ½ to 6 hours
- Safe and gentle for kids

For ages 2-11 years

Watermelon Flavor

Naturally and Artificially Flavored

30 Chewable Tablets

IMPORTANT:Keep this carton for future reference on full labeling.

Poop Should Just Happen.

These tablets are designed for quick, yet gentle relief in 30 minutes to 6 hours. Tasty watermelon-flavored chewable tablets are appropriately dosed for children and allow relief without the painful cramping sometimes associated with stimulant laxatives.

Distributed by:

Wal-Mart Stores, Inc., Bentonville, AR 72716

*This product is not manufactured or distributed by C.B. Fleet Company Inc., the distributor of Pedia-Lax®.